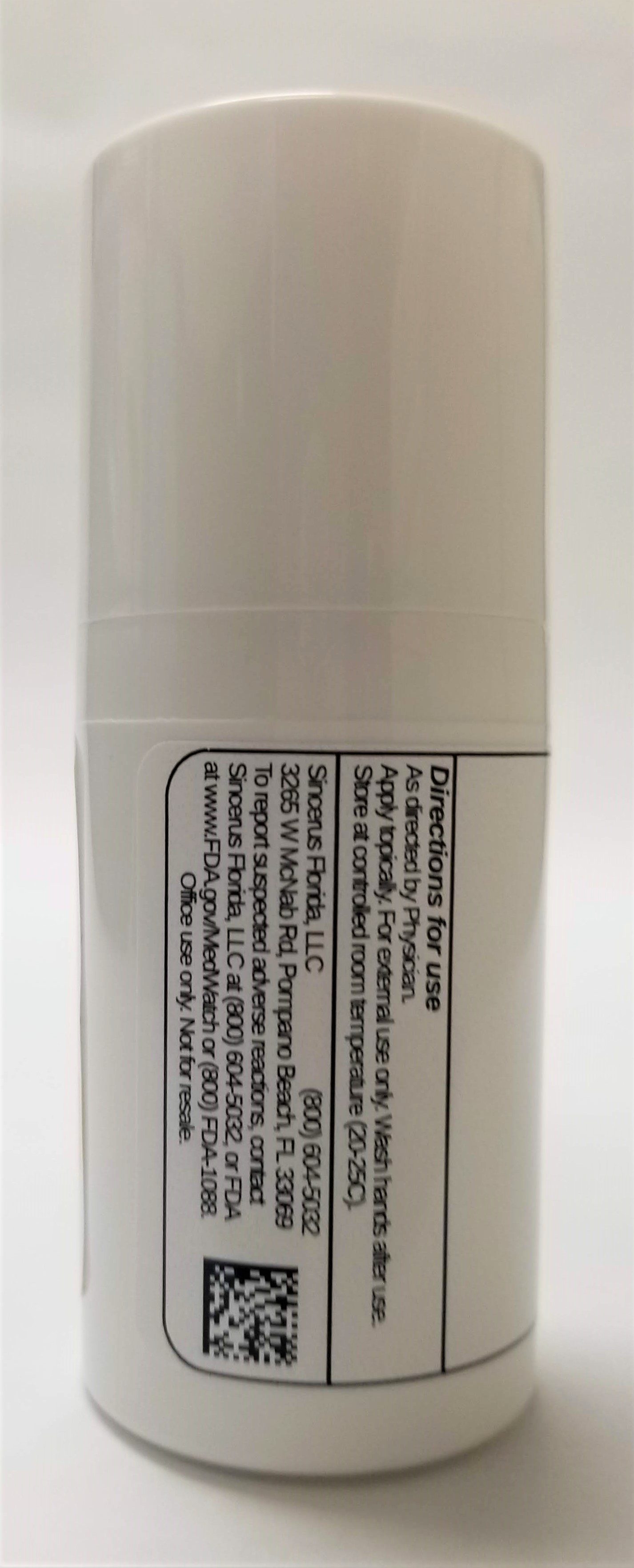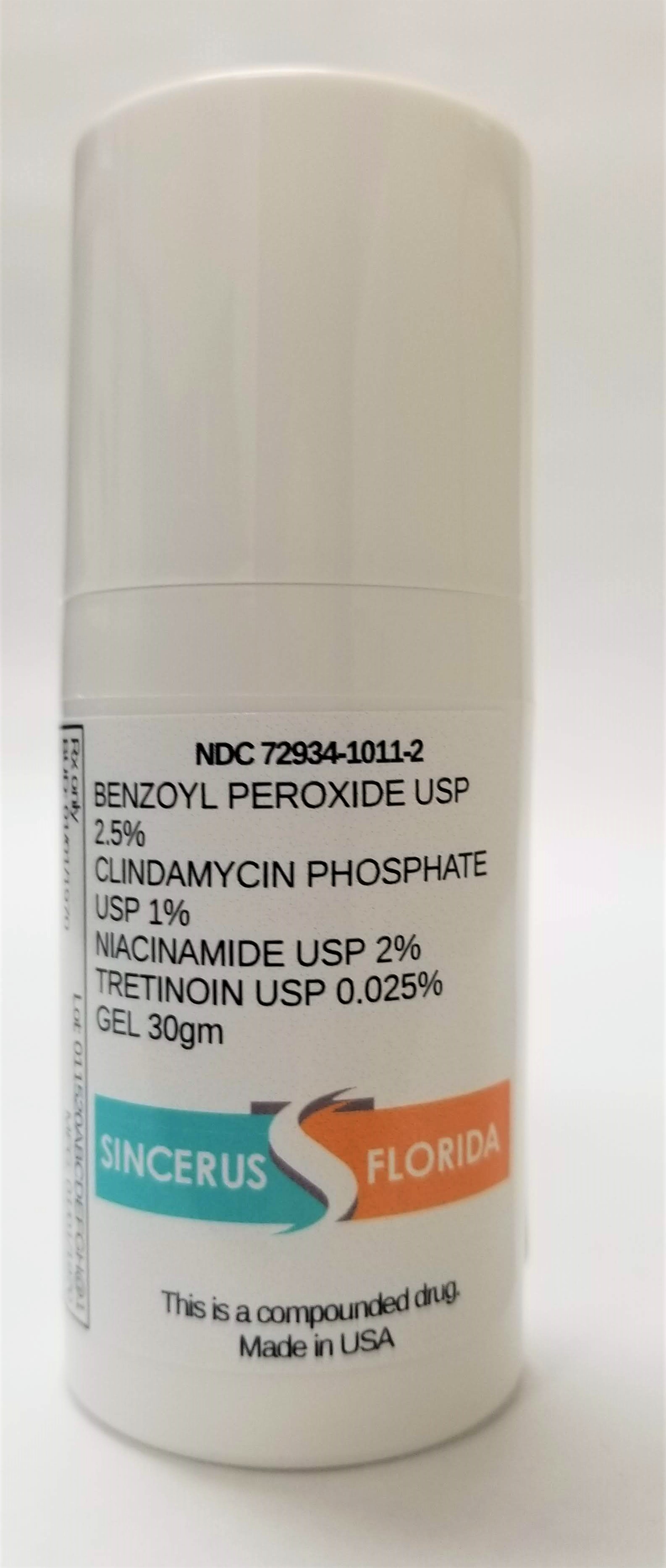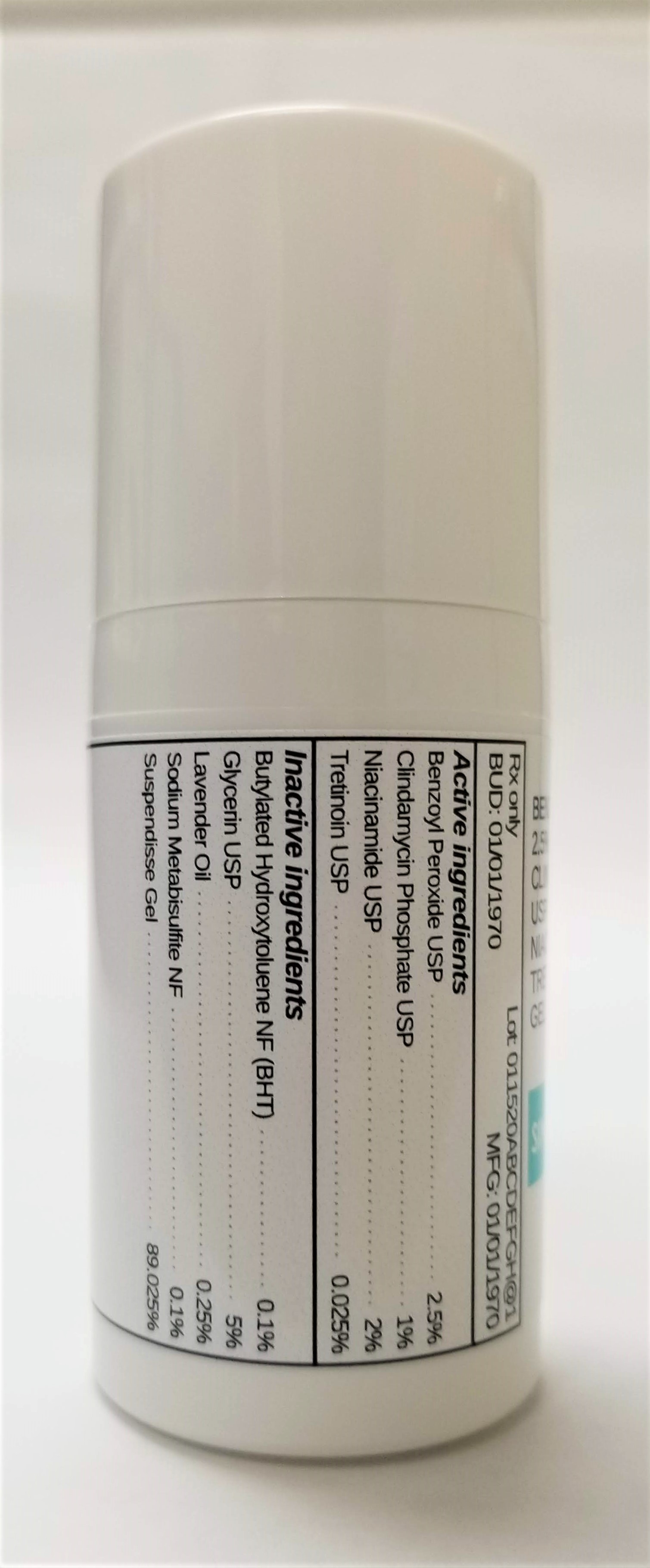 DRUG LABEL: IMIQUIMOD 5% / LEVOCETIRIZINE DIHYDROCHLORIDE 1% / TRETINOIN 0.05%
NDC: 72934-1011 | Form: GEL
Manufacturer: Sincerus Florida, LLC
Category: prescription | Type: HUMAN PRESCRIPTION DRUG LABEL
Date: 20190423

ACTIVE INGREDIENTS: TRETINOIN 0.025 g/100 g; BENZOYL PEROXIDE 2.5 g/100 g; CLINDAMYCIN PHOSPHATE 1 g/100 g; NIACINAMIDE 2 GBq/100 g

IMIQUIMOD 5% / LEVOCETIRIZINE DIHYDROCHLORIDE 1% / TRETINOIN 0.05%